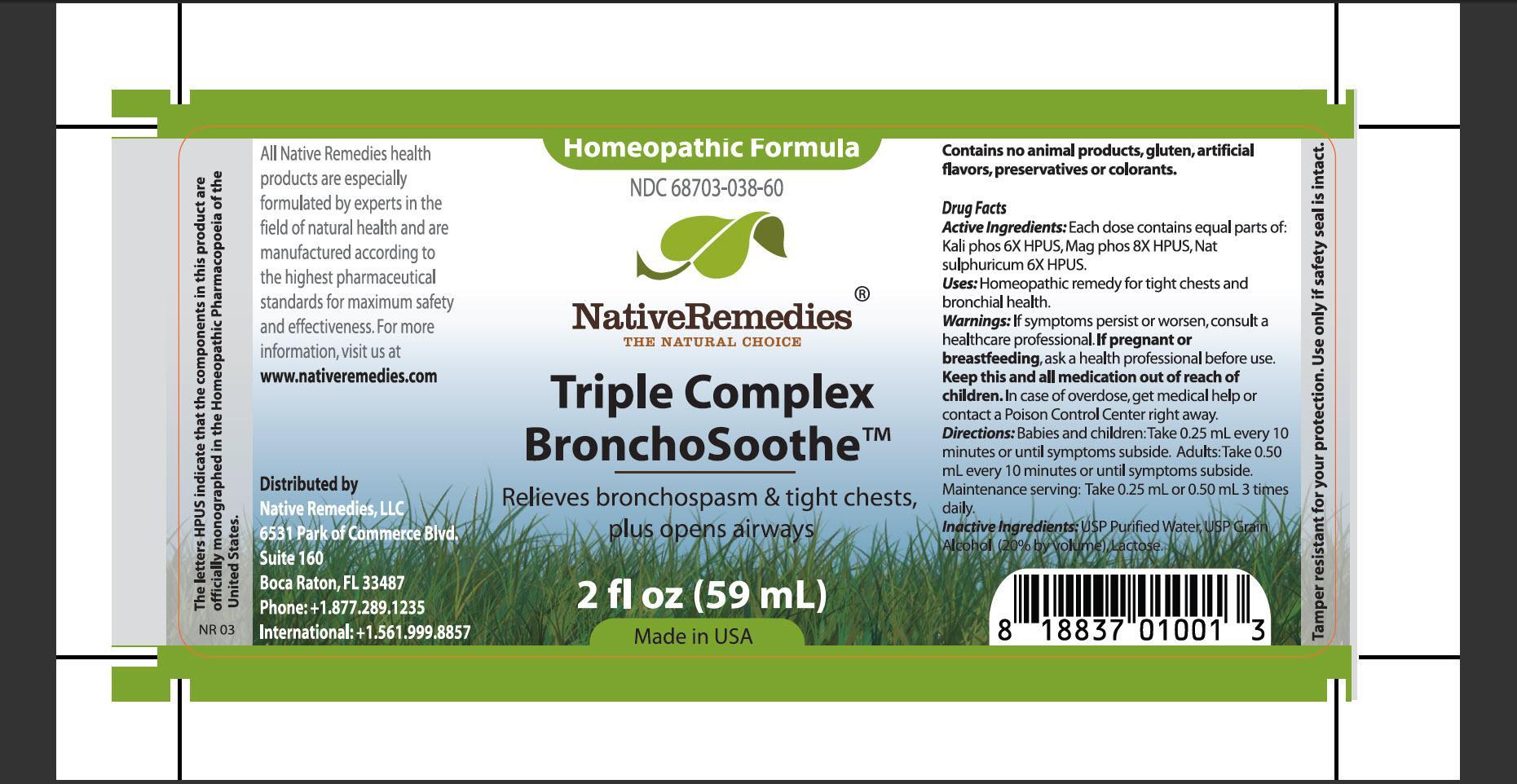 DRUG LABEL: Triple Complex BronchoSoothe
NDC: 68703-038 | Form: TINCTURE
Manufacturer: Native Remedies, LLC
Category: homeopathic | Type: HUMAN OTC DRUG LABEL
Date: 20130320

ACTIVE INGREDIENTS: POTASSIUM PHOSPHATE, DIBASIC 6 [hp_X]/1 mL; MAGNESIUM PHOSPHATE, DIBASIC TRIHYDRATE 8 [hp_X]/1 mL; SODIUM SULFATE 6 [hp_X]/1 mL
INACTIVE INGREDIENTS: WATER; ALCOHOL; LACTOSE

Triple Complex BronchoSoothe

PURPOSE

Relieves bronchospasm and tight chects, plus opens airways

ACTIVE INGREDIENT

Active Ingredients: Each dose contains equal parts of: Kali phos 6X HPUS, Mag phos 8X HPUS, Nat sulphuricum 6X HPUS

INDICATIONS AND USAGE

Uses: Homeopathic remedy for tight chests and bronchial health

WARNINGS

Warnings: If symptoms persist or worsen, consult a healthcare professional

PREGNANCY OR BREAST FEEDING

If pregnant of breastfeeding, ask a health professional before use

KEEP OUT OF REACH OF CHILDREN

Keep this and all medication out of reach of children

OVERDOSAGE

In case of overdose, get medical help of contact a Poison Control Center right away

DOSAGE AND ADMINISTRATION

Directions: Babies and children: Take 0.25 mL every 10 minutes or until symptoms subside. Adults: Take 0.50 mL every 10 minutes or until symptoms subside. Maintenance serving: Take 0.25 mL or 0.50 mL 3 times daily

INACTIVE INGREDIENT

Inactive Ingredients: USP Purified Water, USP Grain Alcohol (20% by volumen), Lactose

PATIENT COUNSELING INFORMATION

The letters HPUS indicate that the components in this product are officially monographed in the Homeopathic Pharmacopoeia of the United States

All Native Remedies health products are especially formulated by experts in the field of natural health and are manufactured according to the highest pharmaceutical standards for maximum safety and effectiveness. For more information, visit us at www.nativeremedies.com

Distributed by
Native Remedies, LLC
6531 Park of Commerce Blvd.
Suite 160
Boca Raton, Fl 33487
Phone: +1.877.289.1235
International:+1.561.999.8857

Contains no animal products, gluten, artificial flavors, preservatives or colorants

STORAGE AND HANDLING

Tamper resistant for your protection. Use only if safety seal is intact